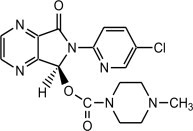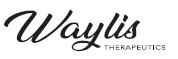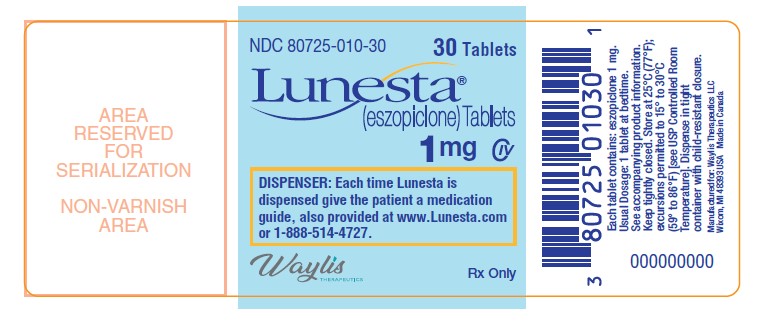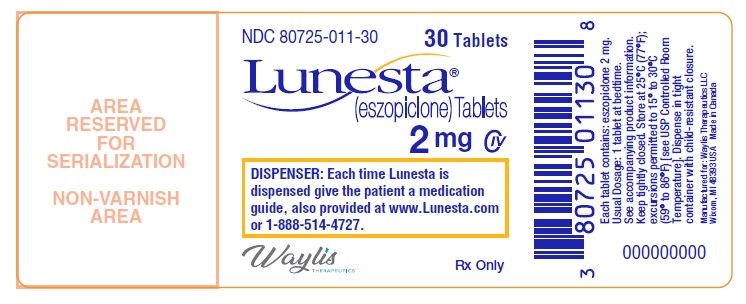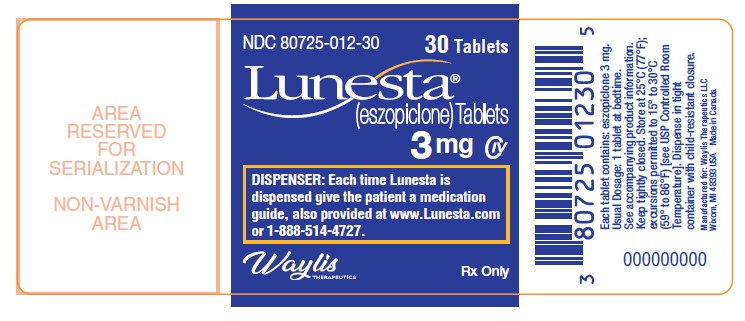 DRUG LABEL: Lunesta
NDC: 80725-010 | Form: TABLET, COATED
Manufacturer: Waylis Therapeutics LLC
Category: prescription | Type: HUMAN PRESCRIPTION DRUG LABEL
Date: 20250108
DEA Schedule: CIV

ACTIVE INGREDIENTS: ESZOPICLONE 1 mg/1 1
INACTIVE INGREDIENTS: CALCIUM PHOSPHATE, DIBASIC, ANHYDROUS; SILICON DIOXIDE; CROSCARMELLOSE SODIUM; HYPROMELLOSE 2910 (6 MPA.S); LACTOSE MONOHYDRATE; MAGNESIUM STEARATE; CELLULOSE, MICROCRYSTALLINE; POLYETHYLENE GLYCOL, UNSPECIFIED; TITANIUM DIOXIDE; TRIACETIN; FD&C BLUE NO. 2

HIGHLIGHTS OF PRESCRIBING INFORMATION

These highlights do not include all the information needed to use LUNESTA safely and effectively. See full prescribing information for LUNESTA.
LUNESTA® (eszopiclone) tablets, for oral use, CIV Initial U.S. Approval: 2004

RECENT MAJOR CHANGES

Boxed Warning | 08/2019
Contraindications (4) | 08/2019
Warnings and Precautions, Complex Sleep Behaviors (5.1) | 08/2019
Warnings and Precautions, CNS Depressant Effects and Next-Day Impairment (5.2) | 12/2018

WARNING: COMPLEX SLEEP BEHAVIORS

See full prescribing information for complete boxed warning.

Complex sleep behaviors including sleep-walking, sleep-driving, and engaging in other activities while not fully awake may occur following use of LUNESTA. Some of these events may result in serious injuries, including death. Discontinue LUNESTA immediately if a patient experiences a complex sleep behavior (4, 5.1).

1 INDICATIONS AND USAGE

LUNESTA is indicated for the treatment of insomnia. LUNESTA has been shown to decrease sleep latency and improve sleep maintenance (1)

2 DOSAGE AND ADMINISTRATION

- Use the lowest dose effective for the patient (2)
- Recommended initial dose is 1 mg, immediately before bedtime, with at least 7-8 hours remaining before the planned time of awakening. May increase dose if clinically indicated, to a maximum of 3 mg (2.1)
- Geriatric or debilitated patients: Dose should not exceed 2 mg (2.2)
- Patients with severe hepatic impairment, or taking potent CYP3A4 inhibitors: Dose should not exceed 2 mg (2.3)
- Do not take with or immediately after a meal (2.5)

3 DOSAGE FORMS AND STRENGTHS

Tablets: 1 mg, 2 mg, and 3 mg (3)

4 CONTRAINDICATIONS

- Patients who have experienced complex sleep behaviors after taking LUNESTA (4)
- Known hypersensitivity to eszopiclone (4)

5 WARNINGS AND PRECAUTIONS

- CNS Depressant Effects: Impaired alertness and motor coordination, including risk of morning impairment. Risk increases with dose and use with other CNS depressants and alcohol. Caution patients taking 3 mg dose against driving and against activities requiring complete mental alertness during the morning after use. (5.2)
- Evaluate for Comorbid Diagnoses: Reevaluate if insomnia persists after 7 to 10 days of use (5.3)
- Severe Anaphylactic/Anaphylactoid Reactions (angioedema and anaphylaxis have been reported): Do not rechallenge if such reactions occur (5.4)
- Abnormal Thinking and Behavioral Changes: Changes including decreased inhibition, bizarre behavior, agitation and depersonalization have been reported. Immediately evaluate any new onset of behavioral changes (5.5)
- Worsening of Depression or Suicidal Thinking may occur: Prescribe the least number of tablets feasible to avoid intentional overdose (5.5, 5.8)
- Withdrawal Effects: Symptoms may occur with rapid dose reduction or discontinuation (5.6, 9.3)
- Elderly Patients: Use lower dose due to impaired motor, cognitive performance and increased sensitivity (2.2, 5.8)
- Patients with Hepatic Impairment, Impaired Respiratory Function, Impaired Drug Metabolism or Hemodynamic Responses: Use with caution (5.8)

6 ADVERSE REACTIONS

Most commonly observed adverse reactions (incidence ≥2%) were unpleasant taste, headache, somnolence, respiratory infection, dizziness, dry mouth, rash, anxiety, hallucinations, and viral infections (6.1)

To report SUSPECTED ADVERSE REACTIONS, contact Waylis Therapeutics LLC at 888-514-4727 or FDA at 1-800-FDA-1088 or www.fda.gov/medwatch.

7 DRUG INTERACTIONS

- CNS Depressants: Additive CNS-depressant effects with combination use. Use with ethanol causes additive psychomotor impairment (7.1)
- Rifampicin: Combination use may decrease exposure and effects of LUNESTA (7.2)
- Ketoconazole: Combination use increases exposure and effect of LUNESTA. Dose reduction of LUNESTA is needed (7.2)

8 USE IN SPECIFIC POPULATIONS

- Pediatric Use: Safety and effectiveness not established. Dizziness, dysgeusia, hallucinations, suicidal ideation reported (8.4)

FULL PRESCRIBING INFORMATION

WARNING: COMPLEX SLEEP BEHAVIORS

Complex sleep behaviors including sleep-walking, sleep-driving, and engaging in other activities while not fully awake may occur following use of LUNESTA. Some of these events may result in serious injuries, including death. Discontinue LUNESTA immediately if a patient experiences a complex sleep behavior [see Contraindications (4) and Warnings and Precautions (5.1)].

1 INDICATIONS AND USAGE

LUNESTA® (eszopiclone) is indicated for the treatment of insomnia. In controlled outpatient and sleep laboratory studies, LUNESTA administered at bedtime decreased sleep latency and improved sleep maintenance.

The clinical trials performed in support of efficacy were up to 6 months in duration. The final formal assessments of sleep latency and maintenance were performed at 4 weeks in the 6-week study (adults only), at the end of both 2-week studies (elderly only) and at the end of the 6-month study (adults only).

2 DOSAGE AND ADMINISTRATION

Use the lowest effective dose for the patient.

2.1 Dosage in Adults

The recommended starting dose is 1 mg. Dosing can be raised to 2 mg or 3 mg if clinically indicated. In some patients, the higher morning blood levels of LUNESTA following use of the 2 mg or 3 mg dose increase the risk of next day impairment of driving and other activities that require full alertness [see Warnings and Precautions (5.1)]. The total dose of LUNESTA should not exceed 3 mg, once daily immediately before bedtime [see Warnings and Precautions (5.6)].

2.2 Geriatric or Debilitated Patients

The total dose of LUNESTA should not exceed 2 mg in elderly or debilitated patients.

2.3 Patients with Severe Hepatic Impairment, or Taking Potent CYP3A4 Inhibitors

In patients with severe hepatic impairment, or in patients coadministered LUNESTA with potent CYP3A4 inhibitors, the total dose of LUNESTA should not exceed 2 mg [see Warnings and Precautions (5.7)].

2.4 Use with CNS Depressants

Dosage adjustments may be necessary when LUNESTA is combined with other central nervous system (CNS) depressant drugs because of the potentially additive effects [see Warnings and Precautions (5.1)].

2.5 Administration with Food

Taking LUNESTA with or immediately after a heavy, high-fat meal results in slower absorption and would be expected to reduce the effect of LUNESTA on sleep latency [see Clinical Pharmacology (12.3)].

3 DOSAGE FORMS AND STRENGTHS

LUNESTA is available in 1 mg, 2 mg and 3 mg strengths for oral administration.

LUNESTA 3 mg tablets are round, dark blue, film-coated, and identified with debossed markings of S193 on one side.

LUNESTA 2 mg tablets are round, white, film-coated, and identified with debossed markings of S191 on one side.

LUNESTA 1 mg tablets are round, light blue, film-coated, and identified with debossed markings of S190 on one side.

4 CONTRAINDICATIONS

LUNESTA is contraindicated in patients who have experienced complex sleep behaviors after taking LUNESTA [see Warnings and Precautions (5.1)].

LUNESTA is contraindicated in patients with known hypersensitivity to eszopiclone. Hypersensitivity reactions include anaphylaxis and angioedema [see Warnings and Precautions (5.3)].

5 WARNINGS AND PRECAUTIONS

5.1 Complex Sleep Behaviors

Complex sleep behaviors including sleep-walking, sleep-driving, and engaging in other activities while not fully awake may occur following the first or any subsequent use of LUNESTA. Patients can be seriously injured or injure others during complex sleep behaviors. Such injuries may result in a fatal outcome. Other complex sleep behaviors (e.g., preparing and eating food, making phone calls, or having sex) have also been reported. Patients usually do not remember these events. Post-marketing reports have shown that complex sleep behaviors may occur with LUNESTA alone at recommended dosages, with or without the concomitant use of alcohol or other CNS depressants [see Drug Interactions (7.1)]. Discontinue LUNESTA immediately if a patient experiences a complex sleep behavior.

5.2 CNS Depressant Effects and Next-Day Impairment

LUNESTA is a CNS depressant and can impair daytime function in some patients at the higher doses (2 mg or 3 mg), even when used as prescribed. Prescribers should monitor for excess depressant effects, but impairment can occur in the absence of symptoms (or even with subjective improvement), and impairment may not be reliably detected by ordinary clinical exam (i.e., less than formal psychomotor testing). While pharmacodynamic tolerance or adaptation to some adverse depressant effects of LUNESTA may develop, patients using 3 mg LUNESTA should be cautioned against driving or engaging in other hazardous activities or activities requiring complete mental alertness the day after use.

Additive effects occur with concomitant use of other CNS depressants (e.g., benzodiazepines, opioids, tricyclic antidepressants, alcohol), including daytime use. Downward dose adjustment of LUNESTA and concomitant CNS depressants should be considered [see Dosage and Administration (2.4)].

The use of LUNESTA with other sedative-hypnotics at bedtime or the middle of the night is not recommended.

The risk of next-day psychomotor impairment is increased if LUNESTA is taken with less than a full night of sleep remaining (7- to 8 hours); if higher than the recommended dose is taken; if coadministered with other CNS depressants; or coadministered with other drugs that increase the blood levels of eszopiclone [see Dosage and Administration (2.3) and Clinical Studies (14.3)].

Because Lunesta can cause drowsiness and a decreased level of consciousness, patients, particularly the elderly, are at higher risk of falls.

5.3 Need to Evaluate for Comorbid Diagnoses

Because sleep disturbances may be the presenting manifestation of a physical and/or psychiatric disorder, symptomatic treatment of insomnia should be initiated only after a careful evaluation of the patient. The failure of insomnia to remit after 7 to 10 days of treatment may indicate the presence of a primary psychiatric and/or medical illness that should be evaluated. Worsening of insomnia or the emergence of new thinking or behavior abnormalities may be the consequence of an unrecognized psychiatric or physical disorder. Such findings have emerged during the course of treatment with sedative/hypnotic drugs, including LUNESTA. Because some of the important adverse effects of LUNESTA appear to be dose related, it is important to use the lowest possible effective dose, especially in the elderly [see Dosage and Administration (2.1)].

5.4 Severe Anaphylactic and Anaphylactoid Reactions

Rare cases of angioedema involving the tongue, glottis or larynx have been reported in patients after taking the first or subsequent doses of sedative-hypnotics, including LUNESTA. Some patients have had additional symptoms such as dyspnea, throat closing, or nausea and vomiting that suggest anaphylaxis. Some patients have required medical therapy in the emergency department. If angioedema involves the tongue, glottis or larynx, airway obstruction may occur and be fatal. Patients who develop angioedema after treatment with LUNESTA should not be rechallenged with the drug.

5.5 Abnormal Thinking and Behavioral Changes

A variety of abnormal thinking and behavior changes have been reported to occur in association with the use of sedative/hypnotics. Some of these changes may be characterized by decreased inhibition (e.g., aggressiveness and extroversion that seem out of character), similar to effects produced by alcohol and other CNS depressants. Other reported behavioral changes have included bizarre behavior, agitation, hallucinations, and depersonalization. Amnesia and other neuropsychiatric symptoms may occur unpredictably.

It can rarely be determined with certainty whether a particular instance of the abnormal behaviors listed above is drug induced, spontaneous in origin, or a result of an underlying psychiatric or physical disorder. Nonetheless, the emergence of any new behavioral sign or symptom of concern requires careful and immediate evaluation.

5.6 Withdrawal Effects

Following rapid dose decrease or abrupt discontinuation of the use of sedative/hypnotics, there have been reports of signs and symptoms similar to those associated with withdrawal from other CNS-depressant drugs [see Drug Abuse and Dependence (9)].

5.7 Timing of Drug Administration

LUNESTA should be taken immediately before bedtime. Taking a sedative/hypnotic while still up and about may result in short-term memory impairment, hallucinations, impaired coordination, dizziness, and lightheadedness.

5.8 Special Populations

Use in Elderly and/or Debilitated Patients

Impaired motor and/or cognitive performance after repeated exposure or unusual sensitivity to sedative/hypnotic drugs is a concern in the treatment of elderly and/or debilitated patients. The dose should not exceed 2 mg in elderly or debilitated patients [see Dosage and Administration (2.2)].

Use in Patients with Concomitant Illness

Clinical experience with eszopiclone in patients with concomitant illness is limited. Eszopiclone should be used with caution in patients with diseases or conditions that could affect metabolism or hemodynamic responses.

A study in healthy volunteers did not reveal respiratory-depressant effects at doses 2.5-fold higher (7 mg) than the recommended dose of eszopiclone. Caution is advised, however, if LUNESTA is prescribed to patients with compromised respiratory function.

The dose of LUNESTA should not exceed 2 mg in patients with severe hepatic impairment, because systemic exposure is doubled in such subjects. No dose adjustment appears necessary for subjects with mild or moderate hepatic impairment. No dose adjustment appears necessary in subjects with any degree of renal impairment, since less than 10% of eszopiclone is excreted unchanged in the urine.

The dose of LUNESTA should be reduced in patients who are administered potent inhibitors of CYP3A4, such as ketoconazole, while taking LUNESTA. Downward dose adjustment is also recommended when LUNESTA is administered with agents having known CNS-depressant effects.

Use in Patients with Depression

In primarily depressed patients treated with sedative-hypnotics, worsening of depression, including suicidal thoughts and actions (including completed suicides), have been reported in association with the use of sedative/hypnotics.

Sedative/hypnotic drugs should be administered with caution to patients exhibiting signs and symptoms of depression. Suicidal tendencies may be present in such patients, and protective measures may be required. Intentional overdose is more common in this group of patients; therefore, the least amount of drug that is feasible should be prescribed for the patient at any one time.

6 ADVERSE REACTIONS

The following are described in more detail in the Warnings and Precautions section of the label:

- Complex Sleep Behaviors [see Boxed Warning and Warnings and Precautions (5.1)]
- CNS Depressant Effects and Next-Day Impairment [see Warnings and Precautions (5.2)]
- Need to Evaluate for Comorbid Diagnoses [see Warnings and Precautions (5.3)]
- Severe Anaphylactic and Anaphylactoid Reactions [see Warnings and Precautions (5.4)]
- Abnormal Thinking and Behavioral Changes [see Warnings and Precautions (5.5)]
- Withdrawal Effects [see Warnings and Precautions (5.6)]
- Timing of Drug Administration [see Warnings and Precautions (5.7)]
- Special Populations [see Warnings and Precautions (5.8)]

Because clinical trials are conducted under widely varying conditions, adverse reaction rates observed in the clinical trials of a drug cannot be directly compared to rates in the clinical trials of another drug and may not reflect the rates observed in clinical practice.

The premarketing development program for LUNESTA included eszopiclone exposures in patients and/or normal subjects from two different groups of studies: approximately 400 normal subjects in clinical pharmacology/pharmacokinetic studies, and approximately 1550 patients in placebo-controlled clinical effectiveness studies, corresponding to approximately 263 patient-exposure years. The conditions and duration of treatment with LUNESTA varied greatly and included (in overlapping categories) open-label and double-blind phases of studies, inpatients and outpatients, and short-term and longer-term exposure. Adverse reactions were assessed by collecting adverse events, results of physical examinations, vital signs, weights, laboratory analyses, and ECGs.

The stated frequencies of adverse reactions represent the proportion of individuals who experienced, at least once, adverse reaction of the type listed. A reaction was considered treatment-emergent if it occurred for the first time or worsened while the patient was receiving therapy following baseline evaluation.

6.1 Clinical Trials Experience

Adverse Reactions Resulting in Discontinuation of Treatment

In placebo-controlled, parallel-group clinical trials in the elderly, 3.8% of 208 patients who received placebo, 2.3% of 215 patients who received 2 mg LUNESTA, and 1.4% of 72 patients who received 1 mg LUNESTA discontinued treatment due to an adverse reaction. In the 6-week parallel-group study in adults, no patients in the 3 mg arm discontinued because of an adverse reaction. In the long-term 6-month study in adult insomnia patients, 7.2% of 195 patients who received placebo and 12.8% of 593 patients who received 3 mg LUNESTA discontinued due to an adverse reaction. No reaction that resulted in discontinuation occurred at a rate of greater than 2%.

Adverse Reactions Observed at an Incidence of ≥2% in Controlled Trials

Table 1 shows the incidence of adverse reactions from a Phase 3 placebo-controlled study of LUNESTA at doses of 2 or 3 mg in nonelderly adults. Treatment duration in this trial was 44 days. The table includes only reactions that occurred in 2% or more of patients treated with LUNESTA 2 mg or 3 mg in which the incidence in patients treated with LUNESTA was greater than the incidence in placebo-treated patients.

Table 1: Incidence (%) of Adverse Reactions in a 6-Week Placebo-Controlled Study in Nonelderly Adults with LUNESTA^1
Adverse Reaction | Placebo (n=99) | LUNESTA 2 mg (n=104) | LUNESTA 3 mg (n=105)
Body as a Whole
Headache | 13 | 21 | 17
Viral Infection | 1 | 3 | 3
Digestive System
Dry Mouth | 3 | 5 | 7
Dyspepsia | 4 | 4 | 5
Nausea | 4 | 5 | 4
Vomiting | 1 | 3 | 0
Nervous System
Anxiety | 0 | 3 | 1
Confusion | 0 | 0 | 3
Depression | 0 | 4 | 1
Dizziness | 4 | 5 | 7
Hallucinations | 0 | 1 | 3
Libido Decreased | 0 | 0 | 3
Nervousness | 3 | 5 | 0
Somnolence | 3 | 10 | 8
Respiratory System
Infection | 3 | 5 | 10
Skin and Appendages
Rash | 1 | 3 | 4
Special Senses
Unpleasant Taste | 3 | 17 | 34
Urogenital System
Dysmenorrhea * | 0 | 3 | 0
Gynecomastia ** | 0 | 3 | 0
^1 Reactions for which the LUNESTA incidence was equal to or less than placebo are not listed on the table, but included the following: abnormal dreams, accidental injury, back pain, diarrhea, flu syndrome, myalgia, pain, pharyngitis, and rhinitis.
* Gender-specific adverse reaction in females
** Gender-specific adverse reaction in males

Adverse reactions from Table 1 that suggest a dose-response relationship in adults include viral infection, dry mouth, dizziness, hallucinations, infection, rash, and unpleasant taste, with this relationship clearest for unpleasant taste.

Table 2 shows the incidence of adverse reactions from combined Phase 3 placebo-controlled studies of LUNESTA at doses of 1 or 2 mg in elderly adults (ages 65-86). Treatment duration in these trials was 14 days. The table includes only reactions that occurred in 2% or more of patients treated with LUNESTA 1 mg or 2 mg in which the incidence in patients treated with LUNESTA was greater than the incidence in placebo-treated patients.

Table 2: Incidence (%) of Adverse Reactions in Elderly Adults (Ages 65-86 Years) in 2-Week Placebo-Controlled Trials with LUNESTA^1
Adverse Reactions | Placebo (n=208) | LUNESTA 1 mg (n=72) | LUNESTA 2 mg (n=215)
Body as a Whole
Accidental Injury | 1 | 0 | 3
Headache | 14 | 15 | 13
Pain | 2 | 4 | 5
Digestive System
Diarrhea | 2 | 4 | 2
Dry Mouth | 2 | 3 | 7
Dyspepsia | 2 | 6 | 2
Nervous System
Abnormal Dreams | 0 | 3 | 1
Dizziness | 2 | 1 | 6
Nervousness | 1 | 0 | 2
Neuralgia | 0 | 3 | 0
Skin and Appendages
Pruritus | 1 | 4 | 1
Special Senses
Unpleasant Taste | 0 | 8 | 12
Urogenital System
Urinary Tract Infection | 0 | 3 | 0
^1 Reactions for which the LUNESTA incidence was equal to or less than placebo are not listed on the table, but included the following: abdominal pain, asthenia, nausea, rash, and somnolence.

Adverse reactions from Table 2 that suggest a dose-response relationship in elderly adults include pain, dry mouth, and unpleasant taste, with this relationship again clearest for unpleasant taste.

These figures cannot be used to predict the incidence of adverse reactions in the course of usual medical practice because patient characteristics and other factors may differ from those that prevailed in the clinical trials. Similarly, the cited frequencies cannot be compared with figures obtained from other clinical investigations involving different treatments, uses, and investigators. The cited figures, however, do provide the prescribing physician with some basis for estimating the relative contributions of drug and nondrug factors to the adverse reaction incidence rate in the population studied.

Other Reactions Observed During the Premarketing Evaluation of LUNESTA

Following is a list of modified COSTART terms that reflect adverse reactions as defined in the introduction to the Adverse Reactions section and reported by approximately 1550 subjects treated with LUNESTA at doses in the range of 1 to 3.5 mg/day during Phase 2 and 3 clinical trials throughout the United States and Canada. All reported reactions are included except those already listed in Tables 1 and 2 or elsewhere in labeling, minor reactions common in the general population, and reactions unlikely to be drug related. Although the reactions reported occurred during treatment with LUNESTA, they were not necessarily caused by it.

Reactions are further categorized by body system and listed in order of decreasing frequency according to the following definitions: frequent adverse reactions are those that occurred on one or more occasions in at least 1/100 patients; infrequent adverse reactions are those that occurred in fewer than 1/100 patients but in at least 1/1,000 patients; rare adverse reactions are those that occurred in fewer than 1/1,000 patients. Gender-specific reactions are categorized based on their incidence for the appropriate gender.

Body as a Whole: Frequent: chest pain; Infrequent: allergic reaction, cellulitis, face edema, fever, halitosis, heat stroke, hernia, malaise, neck rigidity, photosensitivity.

Cardiovascular System: Frequent: migraine; Infrequent: hypertension; Rare: thrombophlebitis.

Digestive System: Infrequent: anorexia, cholelithiasis, increased appetite, melena, mouth ulceration, thirst, ulcerative stomatitis; Rare: colitis, dysphagia, gastritis, hepatitis, hepatomegaly, liver damage, stomach ulcer, stomatitis, tongue edema, rectal hemorrhage.

Hemic and Lymphatic System: Infrequent: anemia, lymphadenopathy.

Metabolic and Nutritional: Frequent: peripheral edema; Infrequent: hypercholesteremia, weight gain, weight loss; Rare: dehydration, gout, hyperlipemia, hypokalemia.

Musculoskeletal System: Infrequent: arthritis, bursitis, joint disorder (mainly swelling, stiffness, and pain), leg cramps, myasthenia, twitching; Rare: arthrosis, myopathy, ptosis.

Nervous System: Infrequent: agitation, apathy, ataxia, emotional lability, hostility, hypertonia, hypesthesia, incoordination, insomnia, memory impairment, neurosis, nystagmus, paresthesia, reflexes decreased, thinking abnormal (mainly difficulty concentrating), vertigo; Rare: abnormal gait, euphoria, hyperesthesia, hypokinesia, neuritis, neuropathy, stupor, tremor.

Respiratory System: Infrequent: asthma, bronchitis, dyspnea, epistaxis, hiccup, laryngitis.

Skin and Appendages: Infrequent: acne, alopecia, contact dermatitis, dry skin, eczema, skin discoloration, sweating, urticaria; Rare: erythema multiforme, furunculosis, herpes zoster, hirsutism, maculopapular rash, vesiculobullous rash.

Special Senses: Infrequent: conjunctivitis, dry eyes, ear pain, otitis externa, otitis media, tinnitus, vestibular disorder; Rare: hyperacusis, iritis, mydriasis, photophobia.

Urogenital System: Infrequent: amenorrhea, breast engorgement, breast enlargement, breast neoplasm, breast pain, cystitis, dysuria, female lactation, hematuria, kidney calculus, kidney pain, mastitis, menorrhagia, metrorrhagia, urinary frequency, urinary incontinence, uterine hemorrhage, vaginal hemorrhage, vaginitis; Rare: oliguria, pyelonephritis, urethritis.

6.2 Postmarketing Experience

In addition to the adverse reactions observed during clinical trials, dysosmia, an olfactory dysfunction that is characterized by distortion of the sense of smell, has been reported during postmarketing surveillance with LUNESTA. Because this event is reported spontaneously from a population of unknown size, it is not possible to estimate the frequency of this event.

7 DRUG INTERACTIONS

7.1 CNS Active Drugs

Ethanol: An additive effect on psychomotor performance was seen with coadministration of eszopiclone and ethanol [see Warnings and Precautions (5.1, 5.2)].

Olanzapine: Coadministration of eszopiclone and olanzapine produced a decrease in DSST scores. The interaction was pharmacodynamic; there was no alteration in the pharmacokinetics of either drug.

7.2 Drugs that Inhibit or Induce CYP3A4

Drugs that Inhibit CYP3A4 (Ketoconazole)

CYP3A4 is a major metabolic pathway for elimination of eszopiclone. The exposure of eszopiclone was increased by coadministration of ketoconazole, a potent inhibitor of CYP3A4. Other strong inhibitors of CYP3A4 (e.g., itraconazole, clarithromycin, nefazodone, troleandomycin, ritonavir, nelfinavir) would be expected to behave similarly. Dose reduction of LUNESTA is needed for patient co-administered LUNESTA with potent CYP3A4 inhibitors [see Dosage and Administration (2.3)].

Drugs that Induce CYP3A4 (Rifampicin)

Racemic zopiclone exposure was decreased 80% by concomitant use of rifampicin, a potent inducer of CYP3A4. A similar effect would be expected with eszopiclone. Combination use with CYP3A4 inducer may decrease the exposure and effects of LUNESTA.

8 USE IN SPECIFIC POPULATIONS

8.1 Pregnancy

Risk Summary

Available pharmacovigilance data with LUNESTA use in pregnant women are insufficient to identify a drug-associated risk of major birth defects, miscarriage, or adverse maternal or fetal outcomes. In animal reproduction studies conducted in pregnant rats and rabbits throughout organogenesis, there was no evidence of teratogenicity. Administration of eszopiclone to rats throughout pregnancy and lactation resulted in offspring toxicities at all doses tested; the lowest dose was approximately 200 times the maximum recommended human dose (MRHD) of 3 mg/day based on mg/m^2 body surface area (See Data).

The estimated background risk of major birth defects and miscarriage for the indicated population is unknown. All pregnancies have a background risk of birth defect, loss, or other adverse outcomes. In the U.S. general population, the estimated background risk of major birth defects and miscarriage in clinically recognized pregnancies is 2 to 4% and 15 to 20%, respectively.

Data

Animal Data

Oral administration of eszopiclone to pregnant rats (62.5, 125, or 250 mg/kg/day) and rabbits (4, 8, or 16 mg/kg/day) throughout organogenesis showed no evidence of teratogenicity up to the highest doses tested. In rats, reduced fetal weight and increased incidences of skeletal variations and/or delayed ossification were observed at the mid and high doses. The no-observed-effect dose for adverse effects on embryofetal development is 200 times the MRHD of 3 mg/day on a mg/m^2 basis. No effects on embryofetal development were observed in rabbits; the highest dose tested is approximately 100 times the MRHD on a mg/m^2 basis.

Oral administration of eszopiclone (60, 120, or 180 mg/kg/day) to pregnant rats throughout the pregnancy and lactation resulted in increased post-implantation loss, decreased postnatal pup weights and survival, and increased pup startle response at all doses. The lowest dose tested is approximately 200 times the MRHD on a mg/m^2 basis. Eszopiclone had no effects on other developmental measures or reproductive function in the offspring.

8.2 Lactation

Risk Summary

There are no data on the presence of eszopiclone in either human or animal milk, the effects on the breastfed infant, or the effects on milk production. The developmental and health benefits of breastfeeding should be considered along with the mother's clinical need for LUNESTA and any potential adverse effects on the breastfed infant from LUNESTA or from the underlying maternal condition.

8.4 Pediatric Use

Safety and effectiveness of LUNESTA have not been established in pediatric patients. LUNESTA failed to demonstrate efficacy in controlled clinical studies of pediatric patients with Attention-Deficit/Hyperactivity (ADHD) associated insomnia.

In a 12-week controlled study, 483 pediatric patients (aged 6-17 years) with insomnia associated with ADHD (with 65% of the patients using concomitant ADHD treatments) were treated with oral tablets of LUNESTA (1, 2 or 3 mg tablets, n=323), or placebo (n=160). LUNESTA did not significantly decrease latency to persistent sleep, compared to placebo, as measured by polysomnography after 12 weeks of treatment. Psychiatric and nervous system disorders comprised the most frequent treatment-emergent adverse reactions observed with LUNESTA versus placebo and included dysgeusia (9% vs. 1%), dizziness (6% vs. 2%), hallucinations (2% vs. 0%) and suicidal ideation (0.3% vs. 0%). Nine patients on LUNESTA (3%) discontinued treatment due to an adverse reaction compared to 3 patients on placebo (2%).

In studies in which eszopiclone (2 to 300 mg/kg/day) was orally administered to young rats from weaning through sexual maturity, neurobehavioral impairment (altered auditory startle response) and reproductive toxicity (adverse effects on male reproductive organ weights and histopathology) were observed at doses ≥5 mg/kg/day. Delayed sexual maturation was noted in males and females at ≥10 mg/kg/day. The no-effect dose (2 mg/kg) was associated with plasma exposures (AUC) for eszopiclone and metabolite (S)-desmethylzopiclone [(S)-DMZ] approximately 2 times plasma exposures in humans at the MRHD in adults (3 mg/day).

When eszopiclone (doses from 1 to 50 mg/kg/day) was orally administered to young dogs from weaning through sexual maturity, neurotoxicity (convulsions) was observed at doses ≥ 5 mg/kg/day. Hepatotoxicity (elevated liver enzymes and hepatocellular vacuolation and degeneration) and reproductive toxicity (adverse effects on male reproductive organ weights and histopathology) were noted at doses ≥10 mg/kg/day. The no-effect dose (1 mg/kg) was associated with plasma exposures (AUC) to eszopiclone and (S)-DMZ approximately 3 and 2 times, respectively, plasma exposures in humans at the MRHD in adults.

8.5 Geriatric Use

A total of 287 subjects in double-blind, parallel-group, placebo-controlled clinical trials who received eszopiclone were 65 to 86 years of age. The overall pattern of adverse events for elderly subjects (median age = 71 years) in 2-week studies with nighttime dosing of 2 mg eszopiclone was not different from that seen in younger adults [see Adverse Reactions (6)]. LUNESTA 2 mg exhibited significant reduction in sleep latency and improvement in sleep maintenance in the elderly population. Compared with nonelderly adults, subjects 65 years and older had longer elimination and higher total exposure to eszopiclone. Therefore, dose reduction is recommended in elderly patients [see Dosage and Administration (2.2), Clinical Pharmacology (12.3)].

8.6 Hepatic Impairment

No dose adjustment is necessary for patients with mild-to-moderate hepatic impairment. Exposure was increased in severely impaired patients compared with healthy volunteers. The dose of LUNESTA should not exceed 2 mg in patients with severe hepatic impairment. LUNESTA should be used with caution in patients with hepatic impairment [see Dosage and Administration (2.3), Clinical Pharmacology (12.3)].

9 DRUG ABUSE AND DEPENDENCE

9.1 Controlled Substance

LUNESTA is a Schedule IV controlled substance under the Controlled Substances Act. Other substances under the same classification are benzodiazepines and the nonbenzodiazepine hypnotics zaleplon and zolpidem. While eszopiclone is a hypnotic agent with a chemical structure unrelated to benzodiazepines, it shares some of the pharmacologic properties of the benzodiazepines.

9.2 Abuse

Abuse and addiction are separate and distinct from physical dependence and tolerance. Abuse is characterized by misuse of the drug for nonmedical purposes, often in combination with other psychoactive substances. Physical dependence is a state of adaptation that is manifested by a specific withdrawal syndrome that can be produced by abrupt cessation, rapid dose reduction, decreasing blood level of the drug and/or administration of an antagonist. Tolerance is a state of adaptation in which exposure to a drug induces changes that result in a diminution of one or more of the drug's effects over time. Tolerance may occur to both the desired and undesired effects of drugs and may develop at different rates for different effects.

Addiction is a primary, chronic, neurobiological disease with genetic, psychosocial, and environmental factors influencing its development and manifestations. It is characterized by behaviors that include one or more of the following: impaired control over drug use, compulsive use, continued use despite harm, and craving. Drug addiction is a treatable disease, utilizing a multidisciplinary approach, but relapse is common.

In a study of abuse liability conducted in individuals with known histories of benzodiazepine abuse, eszopiclone at doses of 6 and 12 mg produced euphoric effects similar to those of diazepam 20 mg. In this study, at doses 2-fold or greater than the maximum recommended doses, a dose-related increase in reports of amnesia and hallucinations was observed for both LUNESTA and diazepam.

9.3 Dependence

The clinical trial experience with LUNESTA revealed no evidence of a serious withdrawal syndrome. Nevertheless, the following adverse events included in DSM-IV criteria for uncomplicated sedative/hypnotic withdrawal were reported during clinical trials following placebo substitution occurring within 48 hours following the last LUNESTA treatment: anxiety, abnormal dreams, nausea, and upset stomach. These reported adverse events occurred at an incidence of 2% or less. Use of benzodiazepines and similar agents may lead to physical and psychological dependence. The risk of abuse and dependence increases with the dose and duration of treatment and concomitant use of other psychoactive drugs. The risk is also greater for patients who have a history of alcohol or drug abuse or history of psychiatric disorders. These patients should be under careful surveillance when receiving LUNESTA or any other hypnotic.

9.4 Tolerance

Some loss of efficacy to the hypnotic effect of benzodiazepines and benzodiazepine-like agents may develop after repeated use of these drugs for a few weeks.

No development of tolerance to any parameter of sleep measurement was observed over six months. Tolerance to the efficacy of LUNESTA 3 mg was assessed by 4-week objective and 6-week subjective measurements of time to sleep onset and sleep maintenance for LUNESTA in a placebo-controlled 44-day study, and by subjective assessments of time to sleep onset and wake time after sleep onset (WASO) in a placebo-controlled study for 6 months.

10 OVERDOSAGE

In clinical trials with eszopiclone, one case of overdose with up to 36 mg of eszopiclone was reported in which the subject fully recovered. Since commercial marketing began, spontaneous cases of eszopiclone overdoses up to 270 mg (90 times the maximum recommended dose of eszopiclone) have been reported, in which patients have recovered. Fatalities related to LUNESTA overdoses were reported only in combination with other CNS drugs or alcohol.

10.1 Signs and Symptoms

Signs and symptoms of overdose effects of CNS depressants can be expected to present as exaggerations of the pharmacological effects noted in preclinical testing. Impairment of consciousness ranging from somnolence to coma has been described. Rare individual instances of fatal outcomes following overdose with racemic zopiclone have been reported in European postmarketing reports, most often associated with overdose with other CNS-depressant agents. Methemoglobinemia in association with overdoses of racemic zopiclone has been reported.

10.2 Recommended Treatment

General symptomatic and supportive measures should be used along with immediate gastric lavage where appropriate. Intravenous fluids should be administered as needed. Flumazenil may be useful. As in all cases of drug overdose, respiration, pulse, blood pressure, and other appropriate signs should be monitored and general supportive measures employed. Hypotension and CNS depression should be monitored and treated by appropriate medical intervention. Consider monitoring methemoglobin in the setting of high-dose overdosage. The value of dialysis in the treatment of overdosage has not been determined.

As with the management of all overdosage, the possibility of multiple drug ingestion should be considered. The physician may wish to consider contacting a poison control center for up-to-date information on the management of hypnotic drug product overdosage.

11 DESCRIPTION

LUNESTA (eszopiclone) is a nonbenzodiazepine hypnotic agent that is a pyrrolopyrazine derivative of the cyclopyrrolone class. The chemical name of eszopiclone is (+)-(5S)-6-(5-chloropyridin-2-yl)-7-oxo-6,7-dihydro-5H-pyrrolo[3,4-b] pyrazin-5-yl 4-methylpiperazine-1-carboxylate. Its molecular weight is 388.81, and its empirical formula is C17H17ClN6O3. Eszopiclone has a single chiral center with an (S)-configuration. It has the following chemical structure:

Eszopiclone is a white to light-yellow crystalline solid. Eszopiclone is very slightly soluble in water, slightly soluble in ethanol, and soluble in phosphate buffer (pH 3.2).

Eszopiclone is formulated as film-coated tablets for oral administration. LUNESTA tablets contain 1 mg, 2 mg, or 3 mg eszopiclone and the following inactive ingredients: calcium phosphate, colloidal silicon dioxide, croscarmellose sodium, hypromellose, lactose, magnesium stearate, microcrystalline cellulose, polyethylene glycol, titanium dioxide, and triacetin. In addition, both the 1 mg and 3 mg tablets contain FD&C Blue #2.

12 CLINICAL PHARMACOLOGY

12.1 Mechanism of Action

The mechanism of action of eszopiclone as a hypnotic is unclear; however, its effect could be related to its interaction with GABA-receptor complexes at binding domains located close to or allosterically coupled to benzodiazepine receptors.

12.3 Pharmacokinetics

The pharmacokinetics of eszopiclone have been investigated in healthy subjects (adult and elderly) and in patients with hepatic disease or renal disease. In healthy subjects, the pharmacokinetic profile was examined after single doses of up to 7.5 mg and after once-daily administration of 1, 3, and 6 mg for 7 days. Eszopiclone is rapidly absorbed, with a time to peak concentration (tmax) of approximately 1 hour and a terminal-phase elimination half-life (t1/2) of approximately 6 hours. In healthy adults, LUNESTA does not accumulate with once-daily administration, and its exposure is dose-proportional over the range of 1 to 6 mg.

Absorption and Distribution

Eszopiclone is rapidly absorbed following oral administration. Peak plasma concentrations are achieved within approximately 1 hour after oral administration. Eszopiclone is weakly bound to plasma protein (52-59%). The large free fraction suggests that eszopiclone disposition should not be affected by drug-drug interactions caused by protein binding. The blood-to-plasma ratio for eszopiclone is less than one, indicating no selective uptake by red blood cells.

Metabolism

Following oral administration, eszopiclone is extensively metabolized by oxidation and demethylation. The primary plasma metabolites are (S)-zopiclone-N-oxide and (S)-N-desmethyl zopiclone; the latter compound binds to GABA receptors with substantially lower potency than eszopiclone, and the former compound shows no significant binding to this receptor. In vitro studies have shown that CYP3A4 and CYP2E1 enzymes are involved in the metabolism of eszopiclone. Eszopiclone did not show any inhibitory potential on CYP450 1A2, 2A6, 2C9, 2C19, 2D6, 2E1, and 3A4 in cryopreserved human hepatocytes.

Elimination

After oral administration, eszopiclone is eliminated with a mean t1/2 of approximately 6 hours. Up to 75% of an oral dose of racemic zopiclone is excreted in the urine, primarily as metabolites. A similar excretion profile would be expected for eszopiclone, the S-isomer of racemic zopiclone. Less than 10% of the orally administered eszopiclone dose is excreted in the urine as parent drug.

Effect of Food

In healthy adults, administration of a 3 mg dose of eszopiclone after a high-fat meal resulted in no change in AUC, a reduction in mean Cmax of 21%, and delayed tmax by approximately 1 hour. The half-life remained unchanged, approximately 6 hours. The effects of LUNESTA on sleep onset may be reduced if it is taken with or immediately after a high-fat/heavy meal.

Specific Populations

Age

Compared with nonelderly adults, subjects 65 years and older had an increase of 41% in total exposure (AUC) and a slightly prolonged elimination of eszopiclone (t1/2 approximately 9 hours). Cmax was unchanged. Therefore, in elderly patients the dose should not exceed 2 mg.

Gender

The pharmacokinetics of eszopiclone in men and women are similar.

Race

In an analysis of data on all subjects participating in Phase 1 studies of eszopiclone, the pharmacokinetics for all races studied appeared similar.

Hepatic Impairment

Pharmacokinetics of a 2 mg eszopiclone dose were assessed in 16 healthy volunteers and in 8 subjects with mild, moderate, and severe liver disease. Exposure was increased 2-fold in severely impaired patients compared with the healthy volunteers. Cmax and tmax were unchanged. No dose adjustment is necessary for patients with mild-to-moderate hepatic impairment. Dose reduction is recommended for patients with severe hepatic impairment. LUNESTA should be used with caution in patients with hepatic impairment [see Dosage and Administration (2.3)].

Renal Impairment

The pharmacokinetics of eszopiclone were studied in 24 patients with mild, moderate, or severe renal impairment. AUC and Cmax were similar in the patients compared with demographically matched healthy control subjects. No dose adjustment is necessary in patients with renal impairment, since less than 10% of the orally administered eszopiclone dose is excreted in the urine as parent drug.

Drug Interactions

Eszopiclone is metabolized by CYP3A4 and CYP2E1 via demethylation and oxidation. There were no pharmacokinetic or pharmacodynamic interactions between eszopiclone and paroxetine. When eszopiclone was coadministered with olanzapine, no pharmacokinetic interaction was detected in levels of eszopiclone or olanzapine, but a pharmacodynamic interaction was seen on a measure of psychomotor function. Eszopiclone and lorazepam decreased each other's Cmax by 22%. Coadministration of eszopiclone 3 mg to subjects receiving ketoconazole, a potent inhibitor of CYP3A4, 400 mg daily for 5 days, resulted in a 2.2-fold increase in exposure to eszopiclone. Cmax and t1/2 were increased 1.4-fold and 1.3-fold, respectively. LUNESTA would not be expected to alter the clearance of drugs metabolized by common CYP450 enzymes [see Warnings and Precautions (5.7), Dosage and Administration (2.3)].

Paroxetine: Coadministration of single dose of eszopiclone and paroxetine produced no pharmacokinetic or pharmacodynamic interaction. The lack of a drug interaction following single-dose administration does not predict the complete absence of a pharmacodynamic effect following chronic administration.

Lorazepam: Coadministration of single doses of eszopiclone and lorazepam did not have clinically relevant effects on the pharmacodynamics or pharmacokinetics of either drug. The lack of a drug interaction following single-dose administration does not predict the complete absence of a pharmacodynamic effect following chronic administration.

Drugs with a Narrow Therapeutic Index

Digoxin: A single dose of eszopiclone 3 mg did not affect the pharmacokinetics of digoxin measured at steady state following dosing of 0.5 mg twice daily for one day and 0.25 mg daily for the next 6 days.

Warfarin: Eszopiclone 3 mg administered daily for 5 days did not affect the pharmacokinetics of (R)- or (S)-warfarin, nor were there any changes in the pharmacodynamic profile (prothrombin time) following a single 25 mg oral dose of warfarin.

Drugs Highly Bound to Plasma Protein

Eszopiclone is not highly bound to plasma proteins (52-59% bound); therefore, the disposition of eszopiclone is not expected to be sensitive to alterations in protein binding. Administration of eszopiclone 3 mg to a patient taking another drug that is highly protein-bound would not be expected to cause an alteration in the free concentration of either drug.

13 NONCLINICAL TOXICOLOGY

13.1 Carcinogenesis, Mutagenesis, Impairment of Fertility

Carcinogenesis

In a carcinogenicity study in rats, oral administration of eszopiclone for 97 (males) or 104 (females) weeks resulted in no increases in tumors; plasma levels (AUC) of eszopiclone at the highest dose tested (16 mg/kg/day) are approximately 80 (females) and 20 (males) times those in humans at the MRHD of 3 mg/day. However, in a 2-year carcinogenicity study in rats, oral administration of racemic zopiclone (1, 10, or 100 mg/kg/day) resulted in increases in mammary gland adenocarcinomas (females) and thyroid gland follicular cell adenomas and carcinomas (males) at the highest dose tested. Plasma levels of eszopiclone at this dose are approximately 150 (females) and 70 (males) times those in humans at the MRHD of eszopiclone. The mechanism for the increase in mammary adenocarcinomas is unknown. The increase in thyroid tumors is thought to be due to increased levels of TSH secondary to increased metabolism of circulating thyroid hormones, a mechanism not considered relevant to humans.

In a 2-year carcinogenicity study in mice, oral administration of racemic zopiclone (1, 10, or 100 mg/kg/day) produced increases in pulmonary carcinomas and carcinomas plus adenomas (females) and skin fibromas and sarcomas (males) at the highest dose tested. The skin tumors were due to skin lesions induced by aggressive behavior, a mechanism not relevant to humans. A carcinogenicity study of eszopiclone was conducted in mice at oral doses up to 100 mg/kg/day. Although this study did not reach a maximum tolerated dose, and was thus inadequate for overall assessment of carcinogenic potential, no increases in either pulmonary or skin tumors were seen at doses producing plasma levels of eszopiclone approximately 90 times those in humans at the MRHD of eszopiclone (and 12 times the exposure in the racemate study).

Eszopiclone did not increase tumors in a p53 transgenic mouse bioassay at oral doses up to 300 mg/kg/day.

Mutagenesis

Eszopiclone was clastogenic in in vitro (mouse lymphoma and chromosomal aberration) assays in mammalian cells. Eszopiclone was negative in the in vitro bacterial gene mutation (Ames) assay and in an in vivo micronucleus assay.

(S)-N-desmethyl zopiclone, a metabolite of eszopiclone, was positive in in vitro chromosomal aberration assays in mammalian cells. (S)-N-desmethyl zopiclone was negative in the in vitro bacterial gene mutation (Ames) assay and in an in vivo chromosomal aberration and micronucleus assay.

Impairment of Fertility

Oral administration of eszopiclone to rats prior to and during mating, and continuing in females to day 7 of gestation (doses up to 45 mg/kg/day to males and females or up to 180 mg/kg/day to females only) resulted in decreased fertility, with no pregnancy at the highest dose tested when both males and females were treated. In females, there was an increase in abnormal estrus cycles at the highest dose tested. In males, decreases in sperm number and motility and increases in morphologically abnormal sperm were observed at the mid and high doses. The no-effect dose for adverse effects on fertility (5 mg/kg/day) is 16 times the MRHD on a mg/m^2 basis.

14 CLINICAL STUDIES

The effect of LUNESTA on reducing sleep latency and improving sleep maintenance was established in studies with 2100 subjects (ages 18-86) with chronic and transient insomnia in six placebo-controlled trials of up to 6 months' duration. Two of these trials were in elderly patients (n=523). Overall, at the recommended adult dose (2-3 mg) and elderly dose (1-2 mg), LUNESTA significantly decreased sleep latency and improved measures of sleep maintenance (objectively measured as WASO and subjectively measured as total sleep time).

14.1 Transient Insomnia

Healthy adults were evaluated in a model of transient insomnia (n=436) in a sleep laboratory in a double-blind, parallel-group, single-night trial comparing two doses of eszopiclone and placebo. LUNESTA 3 mg was superior to placebo on measures of sleep latency and sleep maintenance, including polysomnographic (PSG) parameters of latency to persistent sleep (LPS) and WASO.

14.2 Chronic Insomnia (Adults and Elderly)

The effectiveness of LUNESTA was established in five controlled studies in chronic insomnia. Three controlled studies were in adult subjects, and two controlled studies were in elderly subjects with chronic insomnia.

Adults

In the first study, adults with chronic insomnia (n=308) were evaluated in a double-blind, parallel-group trial of 6 weeks' duration comparing LUNESTA 2 mg and 3 mg with placebo. Objective endpoints were measured for 4 weeks. Both 2 mg and 3 mg were superior to placebo on LPS at 4 weeks. The 3 mg dose was superior to placebo on WASO.

In the second study, adults with chronic insomnia (n=788) were evaluated using subjective measures in a double-blind, parallel-group trial comparing the safety and efficacy of LUNESTA 3 mg with placebo administered nightly for 6 months. LUNESTA was superior to placebo on subjective measures of sleep latency, total sleep time, and WASO.

In addition, a 6-period crossover PSG study evaluating eszopiclone doses of 1 to 3 mg, each given over a 2-day period, demonstrated effectiveness of all doses on LPS, and of 3 mg on WASO. In this trial, the response was dose related.

Elderly

Elderly subjects (ages 65-86 years) with chronic insomnia were evaluated in two double-blind, parallel-group trials of 2 weeks duration. One study (n=231) compared the effects of LUNESTA with placebo on subjective outcome measures, and the other (n=292) on objective and subjective outcome measures. The first study compared 1 mg and 2 mg of LUNESTA with placebo, while the second study compared 2 mg of LUNESTA with placebo. All doses were superior to placebo on measures of sleep latency. In both studies, 2 mg of LUNESTA was superior to placebo on measures of sleep maintenance.

14.3 Studies Pertinent to Safety Concerns for Sedative Hypnotic Drugs

Next-Day Residual Effects

In a double-blind study of 91 healthy adults age 25- to 40 years, the effects of LUNESTA 3 mg on psychomotor function were assessed between 7.5 and 11.5 hours the morning after dosing. Measures included tests of psychomotor coordination that are correlated with ability to maintain a motor vehicle in the driving lane, tests of working memory, and subjective perception of sedation and coordination. Compared with placebo, LUNESTA 3 mg was associated with next- morning psychomotor and memory impairment that was most severe at 7.5 hours, but still present and potentially clinically meaningful at 11.5 hours. Subjective perception of sedation and coordination from LUNESTA 3 mg was not consistently different from placebo, even though subjects were objectively impaired.

In a 6-month double-blind, placebo-controlled trial of nightly administered LUNESTA 3 mg, memory impairment was reported by 1.3% (8/593) of subjects treated with LUNESTA 3 mg compared to 0% (0/195) of subjects treated with placebo. In a 6-week adult study of nightly administered LUNESTA confusion was reported by 3.0% of patients treated with LUNESTA 3 mg, compared to 0% of subjects treated with placebo. In the same study, memory impairment was reported by 1% of patients treated with either 2 mg or 3 mg LUNESTA, compared to 0% treated with placebo.

In a 2-week study of 264 elderly insomniacs, 1.5% of patients treated with LUNESTA 2 mg reported memory impairment compared to 0% treated with placebo. In another 2-week study of 231 elderly insomniacs, 2.5% of patients treated with LUNESTA 2 mg reported confusion compared to 0% treated with placebo.

Withdrawal-Emergent Anxiety and Insomnia

During nightly use for an extended period, pharmacodynamic tolerance or adaptation has been observed with other hypnotics. If a drug has a short elimination half-life, it is possible that a relative deficiency of the drug or its active metabolites (i.e., in relationship to the receptor site) may occur at some point in the interval between each night's use. This is believed to be responsible for two clinical findings reported to occur after several weeks of nightly use of other rapidly eliminated hypnotics: increased wakefulness during the last quarter of the night and the appearance of increased signs of daytime anxiety.

In a 6-month double-blind, placebo-controlled study of nightly administration of LUNESTA 3 mg, rates of anxiety reported as an adverse event were 2.1% in the placebo arm and 3.7% in the LUNESTA arm. In a 6-week adult study of nightly administration, anxiety was reported as an adverse event in 0%, 2.9%, and 1.0% of the placebo, 2 mg, and 3 mg treatment arms, respectively. In this study, single-blind placebo was administered on nights 45 and 46, the first and second days of withdrawal from study drug. New adverse events were recorded during the withdrawal period, beginning with day 45, up to 14 days after discontinuation. During this withdrawal period, 105 subjects previously taking nightly LUNESTA 3 mg for 44 nights spontaneously reported anxiety (1%), abnormal dreams (1.9%), hyperesthesia (1%), and neurosis (1%), while none of 99 subjects previously taking placebo reported any of these adverse events during the withdrawal period.

Rebound insomnia, defined as a dose-dependent temporary worsening in sleep parameters (latency, sleep efficiency, and number of awakenings) compared with baseline following discontinuation of treatment, is observed with short- and intermediate-acting hypnotics. Rebound insomnia following discontinuation of LUNESTA relative to placebo and baseline was examined objectively in a 6-week adult study on the first 2 nights of discontinuation (nights 45 and 46) following 44 nights of active treatment with 2 mg or 3 mg. In the LUNESTA 2 mg group, compared with baseline, there was a significant increase in WASO and a decrease in sleep efficiency, both occurring only on the first night after discontinuation of treatment. No changes from baseline were noted in the LUNESTA 3 mg group on the first night after discontinuation, and there was a significant improvement in LPS and sleep efficiency compared with baseline following the second night of discontinuation. Comparisons of changes from baseline between LUNESTA and placebo were also performed. On the first night after discontinuation of LUNESTA 2 mg, LPS and WASO were significantly increased and sleep efficiency was reduced; there were no significant differences on the second night. On the first night following discontinuation of LUNESTA 3 mg, sleep efficiency was significantly reduced. No other differences from placebo were noted in any other sleep parameter on either the first or second night following discontinuation. For both doses, the discontinuation-emergent effect was mild, had the characteristics of the return of the symptoms of chronic insomnia, and appeared to resolve by the second night after LUNESTA discontinuation.

16 HOW SUPPLIED/STORAGE AND HANDLING

LUNESTA 3 mg tablets are round, dark blue, film-coated, and identified with debossed markings of S193 on one side, and are supplied as:

NDC 80725-012-30 bottle of 30 tablets

LUNESTA 2 mg tablets are round, white, film-coated, and identified with debossed markings of S191 on one side, and are supplied as:

NDC 80725-011-30 bottle of 30 tablets

LUNESTA 1 mg tablets are round, light blue, film-coated, and identified with debossed markings of S190 on one side, and are supplied as:

NDC 80725-010-30 bottle of 30 tablets

Store at 25°C (77°F); excursions permitted to 15°C to 30°C (59°F to 86°F) [see USP Controlled Room Temperature].

17 PATIENT COUNSELING INFORMATION

See FDA-approved patient labeling (Medication Guide).

Inform patients and their families about the benefits and risks of treatment with LUNESTA. Inform patients of the availability of a Medication Guide and instruct them to read the Medication Guide prior to initiating treatment with LUNESTA and with each prescription refill. Review the LUNESTA Medication Guide with every patient prior to initiation of treatment. Instruct patients or caregivers that LUNESTA should be taken only as prescribed.

Complex Sleep Behaviors

Instruct patients and their families that LUNESTA may cause complex sleep behaviors, including sleep-walking, sleep-driving, preparing and eating food, making phone calls, or having sex while not being fully awake. Serious injuries and death have occurred during complex sleep behavior episodes. Tell patients to discontinue LUNESTA and notify their healthcare provider immediately if they develop any of these symptoms [see Boxed Warning, Warnings and Precautions (5.1)].

CNS Depressant Effects and Next-Day Impairment

Tell patients that LUNESTA can cause next-day impairment even when used as prescribed, and that this risk is increased if dosing instructions are not carefully followed. Caution patients taking the 3 mg dose against driving and other activities requiring complete mental alertness the day after use. Inform patients that impairment can be present despite feeling fully awake. Advise patients that increased drowsiness and decreased consciousness may increase the risk of falls in some patients [see Warnings and Precautions (5.2)].

Severe Anaphylactic and Anaphylactoid Reactions

Inform patients that severe anaphylactic and anaphylactoid reactions have occurred with eszopiclone. Describe the signs/symptoms of these reactions and advise patients to seek medical attention immediately if any of them occur [see Warnings and Precautions (5.4)].

Suicide

Tell patients to immediately report any suicidal thoughts.

Alcohol and Other Drugs

Ask patients about alcohol consumption, medicines they are taking, and drugs they may be taking without a prescription. Advise patients not to use LUNESTA if they drank alcohol that evening or before bed.

Tolerance, Abuse, and Dependence

Tell patients not to increase the dose of LUNESTA on their own, and to inform you if they believe the drug "does not work."

Administration Instructions

Patients should be counseled to take LUNESTA right before they get into bed and only when they are able to stay in bed a full night (7–8 hours) before being active again. LUNESTA tablets should not be taken with or immediately after a meal. Advise patients NOT to take LUNESTA if they drank alcohol that evening.

Manufactured for:
Waylis Therapeutics LLC
Wixom, MI 48393 USA

MEDICATION GUIDE

LUNESTA® (lū'-nes''-tă) Tablets, Coated C-IV

(eszopiclone)

Read the Medication Guide that comes with LUNESTA before you start taking it and each time you get a refill. There may be new information. This Medication Guide does not take the place of talking to your doctor about your medical condition or treatment.

What is the most important information I should know about LUNESTA?

- Do not take more LUNESTA than prescribed.
- Do not take LUNESTA unless you are able to stay in bed a full night (7 to 8 hours) before you must be active again.
- Take LUNESTA right before you get in bed, not sooner.

LUNESTA may cause serious side effects, including:

Complex sleep behaviors that have caused serious injury and death. After taking LUNESTA, you may get up out of bed while not being fully awake and do an activity that you do not know you are doing (complex sleep behaviors). The next morning, you may not remember that you did anything during the night. These activities may occur with LUNESTA whether or not you drink alcohol or take other medicines that make you sleepy.

Reported activities and behaviors include:

- doing activities when you are asleep like:
  - making and eating food
  - talking on the phone
  - having sex
  - driving a car ("sleep-driving")
  - sleep walking

Stop taking LUNESTA and call your healthcare provider right away if you find out that you have done any of the above activities after taking LUNESTA.

The morning after you take LUNESTA your ability to drive safely and think clearly may be decreased. You also may experience sleepiness during the day.

Do not take LUNESTA if you:

- have ever experienced a complex sleep behavior (such as driving a car, making and eating food, talking on the phone or having sex while not fully awake) after taking LUNESTA
- drank alcohol that evening or before bed
- take other medicines that can make you sleepy. Talk to your doctor about all of your medicines. Your doctor will tell you if you can take LUNESTA with your other medicines.
- cannot get a full night's sleep

_________________________________________________________________________

WHAT IS LUNESTA?

LUNESTA is a sedative-hypnotic (sleep) medicine. LUNESTA is used in adults for the treatment of a sleep problem called insomnia. Symptoms of insomnia include:

- trouble falling asleep
- waking up often during the night

LUNESTA is not for children.

LUNESTA is a federally controlled substance (C-IV) because it can be abused or lead to dependence. Keep LUNESTA in a safe place to prevent misuse and abuse. Selling or giving away LUNESTA may harm others, and is against the law. Tell your doctor if you have ever abused or been dependent on alcohol, prescription medicines or street drugs.

Who should not take LUNESTA?

- Do not take LUNESTA if you have ever had a complex sleep behavior happen after taking LUNESTA.
- Do not take LUNESTA if you are allergic to anything in it. See the end of this Medication Guide for a complete list of ingredients in LUNESTA.

LUNESTA may not be right for you. Before starting LUNESTA, tell your doctor about all of your health conditions, including if you:

- have a history of depression, mental illness, or suicidal thoughts
- have a history of drug or alcohol abuse or addiction
- have liver disease
- are pregnant, planning to become pregnant, or breastfeeding

Tell your doctor about all of the medicines you take including prescription and nonprescription medicines, vitamins and herbal supplements. Medicines can interact with each other, sometimes causing serious side effects. Do not take LUNESTA with other medicines that can make you sleepy.

Know the medicines you take. Keep a list of your medicines with you to show your doctor and pharmacist each time you get a new medicine.

How should I take LUNESTA?

- Take LUNESTA exactly as prescribed. Do not take more LUNESTA than prescribed for you.
- Take LUNESTA right before you get into bed.
- Do not take LUNESTA with or right after a meal.
- Do not take LUNESTA unless you are able to get a full night's sleep before you must be active again.
- Call your doctor if your insomnia worsens or is not better within 7 to 10 days. This may mean that there is another condition causing your sleep problems.
- If you take too much LUNESTA or overdose, call your doctor or poison control center right away, or get emergency treatment.

What are the possible side effects of LUNESTA?

Possible serious side effects of LUNESTA include:

- getting out of bed while not being fully awake and doing an activity that you do not know you are doing. (See “What is the most important information I should know about LUNESTA?”)
- abnormal thoughts and behavior. Symptoms include more outgoing or aggressive behavior than normal, confusion, agitation, acting strangely, hallucinations, worsening of depression, and suicidal thoughts or actions.
- memory loss
- anxiety
- severe allergic reactions. Symptoms include swelling of the tongue or throat, trouble breathing, and nausea and vomiting. Get emergency medical help if you get these symptoms after taking LUNESTA.

Call your doctor right away if you have any of the above side effects or any other side effects that worry you while using LUNESTA.

The most common side effects of LUNESTA are:

- unpleasant taste in mouth, dry mouth
- drowsiness
- dizziness
- headache
- symptoms of the common cold
- You may still feel drowsy the next day after taking LUNESTA. Do not drive or do other dangerous activities after taking LUNESTA until you feel fully awake.

These are not all the side effects of LUNESTA. Ask your doctor or pharmacist for more information. Call your doctor for medical advice about side effects. You may report side effects to FDA at 1-800-FDA-1088.

How should I store LUNESTA?

- Store LUNESTA at room temperature, between 59°F to 86°F (15°C to 30°C).
- Do not use LUNESTA after the expiration date.
- Keep LUNESTA and all medicines out of reach of children.

General Information about LUNESTA

- Medicines are sometimes prescribed for purposes other than those listed in a Medication Guide.
- Do not use LUNESTA for a condition for which it was not prescribed.
- Do not share LUNESTA with other people, even if you think they have the same symptoms that you have. It may harm them and is against the law.

This Medication Guide summarizes the most important information about LUNESTA. If you would like more information, talk with your doctor. You can ask your doctor or pharmacist for information about LUNESTA that is written for healthcare professionals.

- For customer service, call 1-800-689-0255.
- To report side effects or for medical information, call 1-888-514-4727.

What are the ingredients in LUNESTA?

Active Ingredient: eszopiclone

Inactive Ingredients: calcium phosphate, colloidal silicon dioxide, croscarmellose sodium, hypromellose, lactose, magnesium stearate, microcrystalline cellulose, polyethylene glycol, titanium dioxide, and triacetin. In addition, both the 1 mg and 3 mg tablets contain FD&C Blue #2.

This Medication Guide has been approved by the U.S. Food and Drug Administration.

Manufactured for:
Waylis Therapeutics LLC
Wixom, MI 48393 USA

Revised: 07/2023
B-LB1064

1 MG BOTTLE LABEL – PRINCIPAL DISPLAY PANEL – 1mg

NDC 80725-010-30

30 Tablets

Lunesta®

(eszopiclone) Tablets

1 mg C-IV

DISPENSER: Each time Lunesta is

dispensed give the patient a medication

guide, also provided at www.Lunesta.com

or 1-888-514-4727.

Waylis Therapeutics

Rx Only

______________________________________________________________________________

2 MG BOTTLE LABEL – PRINCIPAL DISPLAY PANEL – 2mg

NDC 80725-011-30

30 Tablets

Lunesta®

(eszopiclone) Tablets

2 mg C-IV

DISPENSER: Each time Lunesta is

dispensed give the patient a medication

guide, also provided at www.Lunesta.com

or 1-888-514-4727.

Waylis Therapeutics

Rx Only

3 MG BOTTLE LABEL – PRINCIPAL DISPLAY PANEL – 3mg

NDC 80725-012-03

30 Tablets

Lunesta®

(eszopiclone) Tablets

3 mg C-IV

DISPENSER: Each time Lunesta is

dispensed give the patient a medication

guide, also provided at www.Lunesta.com

or 1-888-514-4727.

Waylis Therapeutics

Rx Only